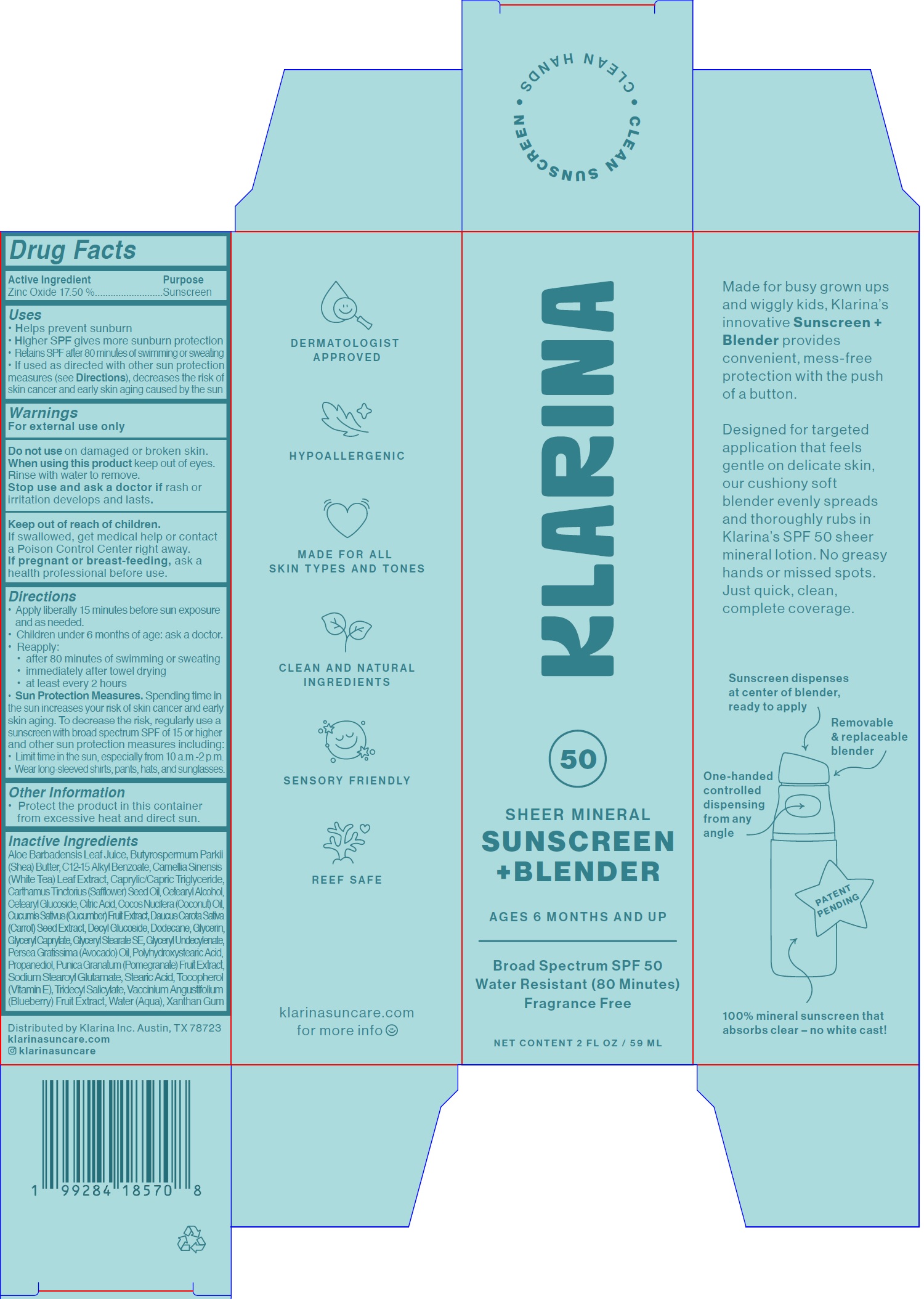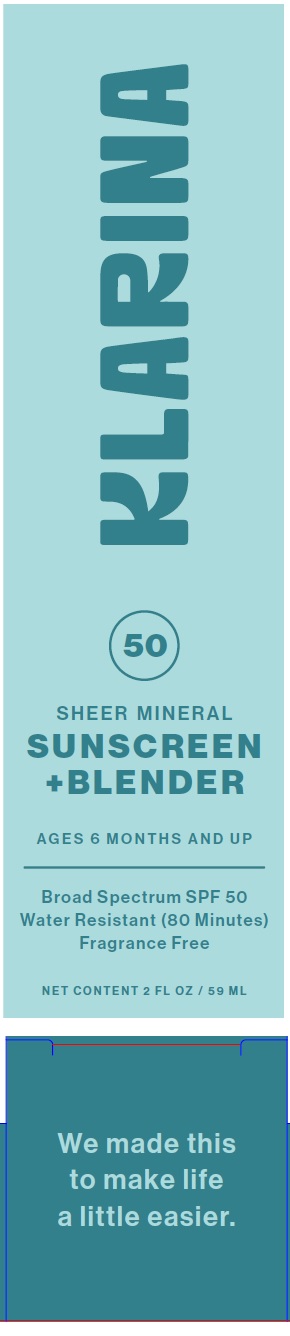 DRUG LABEL: KLARINA Sheer Mineral Sunscreen Blender SPF 50
NDC: 85928-625 | Form: CREAM
Manufacturer: KLARINA INC
Category: otc | Type: HUMAN OTC DRUG LABEL
Date: 20250710

ACTIVE INGREDIENTS: ZINC OXIDE 175 mg/1 mL
INACTIVE INGREDIENTS: ALOE VERA LEAF JUICE; SHEA BUTTER; ALKYL (C12-15) BENZOATE; MEDIUM-CHAIN TRIGLYCERIDES; SAFFLOWER OIL; CETOSTEARYL ALCOHOL; CETEARYL GLUCOSIDE; CITRIC ACID MONOHYDRATE; COCONUT OIL; CUCUMBER; DAUCUS CAROTA SUBSP. SATIVUS SEED; DECYL GLUCOSIDE; DODECANE; GLYCERIN; GLYCERYL MONOCAPRYLATE; GLYCERYL STEARATE SE; AVOCADO OIL; PROPANEDIOL; POMEGRANATE; SODIUM STEAROYL GLUTAMATE; STEARIC ACID; .ALPHA.-TOCOPHEROL; TRIDECYL SALICYLATE; LOWBUSH BLUEBERRY; WATER; XANTHAN GUM

KLARINA Sheer Mineral Sunscreen + Blender SPF 50

Active Ingredient

Zinc Oxide 17.50 %

Purpose

Sunscreen

Uses

• Helps prevent sunburn
• Higher SPF gives more sunburn protection
• Retains SPF after 80 minutes of swimming or sweating
• If used as directed with other sun protection measures (see Directions), decreases the risk of skin cancer and early skin aging caused by the sun

Warnings

For external use only

Do not use

on damaged or broken skin.

When using this product

keep out of eyes. Rinse with water to remove.

Stop use and ask a doctor if

rash or irritation develops and lasts.

Keep out of reach of children.

If swallowed, get medical help or contact a Poison Control Center right away.

If pregnant or breast-feeding,

ask a health professional before use.

Directions

• Apply liberally 15 minutes before sun exposure and as needed.
• Children under 6 months of age: ask a doctor.
• Reapply:
• after 80 minutes of swimming or sweating
• immediately after towel drying
• at least every 2 hours
• Sun Protection Measures.Spending time in the sun increases your risk of skin cancer and early skin aging. To decrease the risk, regularly use a sunscreen with broad spectrum SPF of 15 or higher and other sun protection measures including:
• Limit time in the sun, especially from 10 a.m.-2 p.m.
• Wear long-sleeved shirts, pants, hats, and sunglasses.

Other Information

- Protect the product in this container from excessive heat and direct sun.

Inactive Ingredients

Aloe Barbadensis Leaf Juice, Butyrospermum Parkii (Shea) Butter, C12-15 Alkyl Benzoate, Camellia Sinensis (White Tea) Leaf Extract, Caprylic/Capric Triglyceride, Carthamus Tinctorius (Safflower) Seed Oil, Cetearyl Alcohol, Cetearyl Glucoside, Citric Acid, Cocos Nucifera (Coconut) Oil, Cucumis Sativus (Cucumber) Fruit Extract, Daucus Carota Sativa (Carrot) Seed Extract, Decyl Glucoside, Dodecane, Glycerin, Glyceryl Caprylate, Glyceryl Stearate SE, Glyceryl Undecylenate, Persea Gratissima (Avocado) Oil, Polyhydroxystearic Acid, Propanediol, Punica Granatum (Pomegranate) Fruit Extract, Sodium Stearoyl Glutamate, Stearic Acid, Tocopherol (Vitamin E), Tridecyl Salicylate, Vaccinium Angustifolium (Blueberry) Fruit Extract, Water (Aqua), Xanthan Gum